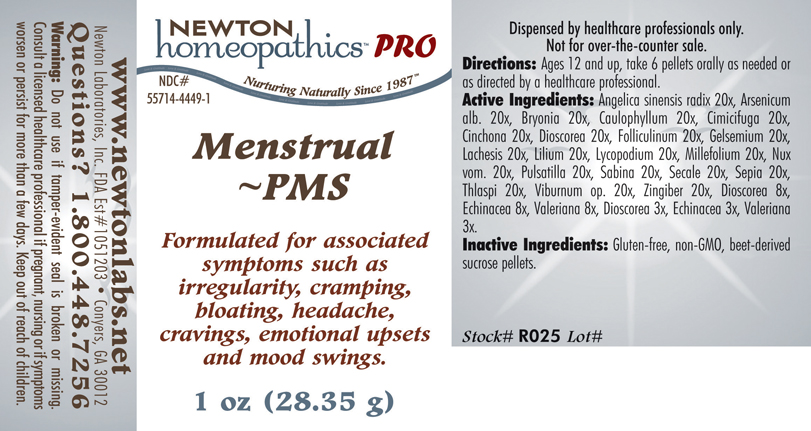 DRUG LABEL: Menstrual - PMS 
NDC: 55714-4449 | Form: PELLET
Manufacturer: Newton Laboratories, Inc.
Category: homeopathic | Type: HUMAN PRESCRIPTION DRUG LABEL
Date: 20110601

ACTIVE INGREDIENTS: Angelica Sinensis Root 20 [hp_X]/1 g; Arsenic Trioxide 20 [hp_X]/1 g; Bryonia Alba Root 20 [hp_X]/1 g; Caulophyllum Thalictroides Root 20 [hp_X]/1 g; Black Cohosh 20 [hp_X]/1 g; Cinchona Officinalis Bark 20 [hp_X]/1 g; Dioscorea Villosa Tuber 20 [hp_X]/1 g; Estrone 20 [hp_X]/1 g; Gelsemium Sempervirens Root 20 [hp_X]/1 g; Lachesis Muta Venom 20 [hp_X]/1 g; Lilium Lancifolium Whole Flowering 20 [hp_X]/1 g; Lycopodium Clavatum Spore 20 [hp_X]/1 g; Achillea Millefolium 20 [hp_X]/1 g; Strychnos Nux-vomica Seed 20 [hp_X]/1 g; Pulsatilla Vulgaris 20 [hp_X]/1 g; Juniperus Sabina Leafy Twig 20 [hp_X]/1 g; Claviceps Purpurea Sclerotium 20 [hp_X]/1 g; Sepia Officinalis Juice 20 [hp_X]/1 g; Capsella Bursa-pastoris 20 [hp_X]/1 g; Viburnum Opulus Bark 20 [hp_X]/1 g; Ginger 20 [hp_X]/1 g; Echinacea, Unspecified 8 [hp_X]/1 g; Valerian 8 [hp_X]/1 g
INACTIVE INGREDIENTS: Sucrose

Menstrual - PMS

INDICATIONS & USAGE SECTION

Menstrual - PMS Formulated for associated symptoms such as irregularity, cramping, bloating, headache, cravings, emotional upsets and mood swings.

DOSAGE & ADMINISTRATION SECTION

Directions: Ages 12 and up, take 6 pellets orally as needed or as directed by a healthcare professional.

ACTIVE INGREDIENT SECTION

Angelica sinensis radix 20x, Arsenicum alb. 20x, Bryonia 20x, Caulophyllum 20x, Cimicifuga 20x, Cinchona 20x, Dioscorea 20x, Folliculinum 20x, Gelsemium 20x, Lachesis 20x, Lilium 20x, Lycopodium 20x, Millefolium 20x, Nux vom. 20x, Pulsatilla 20x, Sabina 20x, Secale 20x, Sepia 20x, Thlaspi 20x, Viburnum op. 20x, Zingiber 20x, Dioscorea 8x, Echinacea 8x, Valeriana 8x, Dioscorea 3x, Echinacea 3x, Valeriana 3x.

PURPOSE SECTION

Formulated for associated symptoms such as irregularity, cramping, bloating, headache, cravings, emotional upsets and mood swings.

INACTIVE INGREDIENT SECTION

Inactive Ingredients: Gluten-free, non-GMO, beet-derived sucrose pellets.

QUESTIONS? SECTION

www.newtonlabs.net Newton Laboratories, Inc. FDA Est # 1051203 - Conyers, GA 30012
Questions? 1.800.448.7256

WARNINGS SECTION

Warning: Do not use if tamper - evident seal is broken or missing. Consult a licensed healthcare professional if pregnant, nursing or if symptoms worsen or persist for more than a few days. Keep out of reach of children.

PREGNANCY OR BREAST FEEDING SECTION

Consult a licensed healthcare professional if pregnant, nursing or if symptoms worsen or persist for more than a few days.

KEEP OUT OF REACH OF CHILDREN SECTION

Keep out of reach of children.